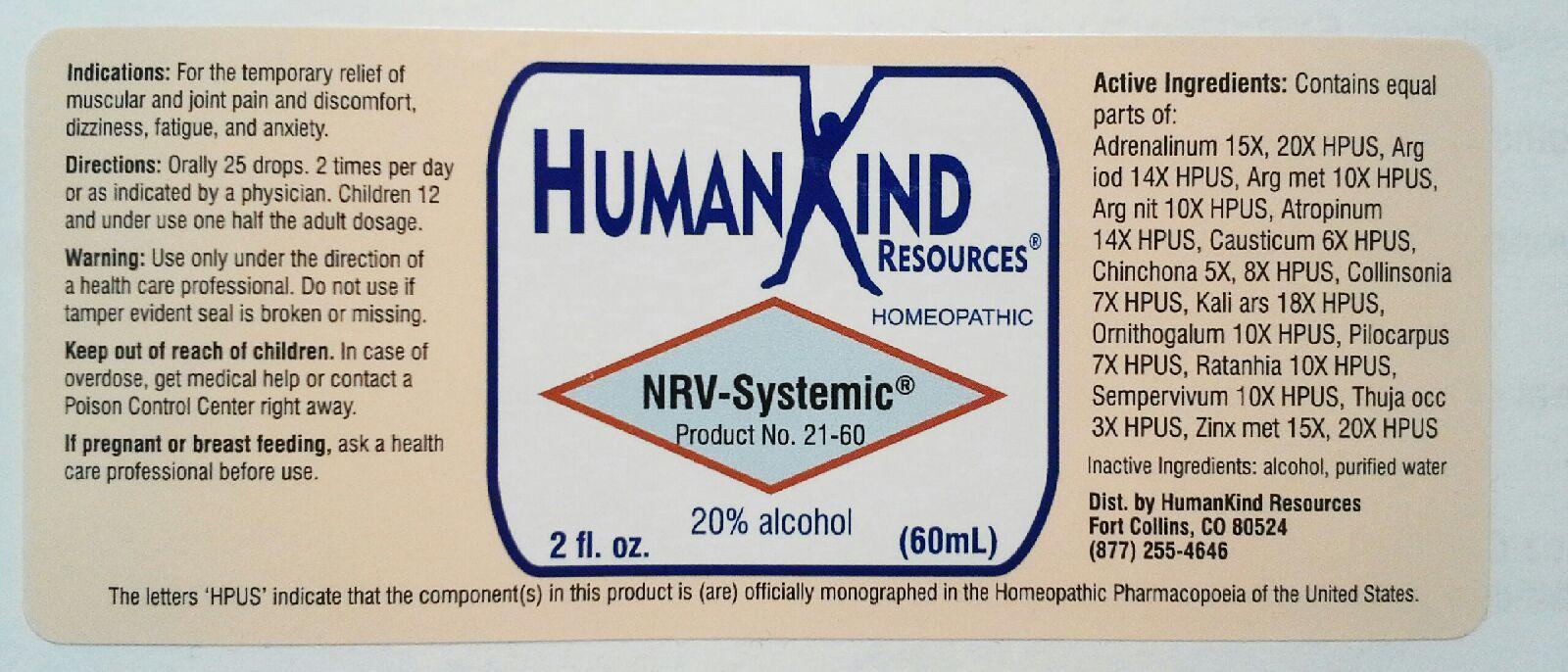 DRUG LABEL: NRV-Systemic
NDC: 64616-099 | Form: LIQUID
Manufacturer: Vitality Works, Inc.
Category: homeopathic | Type: HUMAN OTC DRUG LABEL
Date: 20251217

ACTIVE INGREDIENTS: EPINEPHRINE 20 [hp_X]/1 mL; SILVER IODIDE 14 [hp_X]/1 mL; SILVER 10 [hp_X]/1 mL; SILVER NITRATE 10 [hp_X]/1 mL; ATROPINE 14 [hp_X]/1 mL; CAUSTICUM 6 [hp_X]/1 mL; CINCHONA OFFICINALIS BARK 8 [hp_X]/1 mL; COLLINSONIA CANADENSIS ROOT 7 [hp_X]/1 mL; POTASSIUM ARSENITE ANHYDROUS 18 [hp_X]/1 mL; ORNITHOGALUM UMBELLATUM 10 [hp_X]/1 mL; PILOCARPUS JABORANDI LEAF 7 [hp_X]/1 mL; KRAMERIA LAPPACEA ROOT 10 [hp_X]/1 mL; SEMPERVIVUM TECTORUM LEAF 10 [hp_X]/1 mL; THUJA OCCIDENTALIS LEAFY TWIG 3 [hp_X]/1 mL; ZINC 20 [hp_X]/1 mL
INACTIVE INGREDIENTS: WATER; ALCOHOL

NRV-Systemic

NRV-Systemic

Adrenalinum 15X, 20X Kali Arsenicosum 18X

Argentum Iodatum 14X Ornithogalum Umbellatum 10X

Argentum Metallicum 10X Pilocarpus 7X

Argentum Nitricum 10X Ratanhia 10X

Atropinum 14X Sempervivum Tectorum 10X

Causticum 6X Thuja Occidentalis 3X

Cinchona Officinalis 5X, 8X Zinc Metallicum 15X, 20X

Collinsonia Canadensis 7X

NRV-Systemic

Alcohol, Purified Water

NRV-Systemic

Use only under the direction of a health care professional. Do not use if tamper evident seal is broken or missing.

NRV-Systemic

Keep out of reach of children. In case of overdose, get medical help or contact a Poison Control Center right away.

NRV-Systemic

For the temporary relief of muscular and joint pain and discomfort, dizziness, fatigue and anxiety.

NRV-Systemic

Orally 25 drops, 2 times per day or as indicated by a physician. Children 12 and under use one half the adult dosage.

NRV-Systemic

Aids in balancing and stimulating the nervous system.